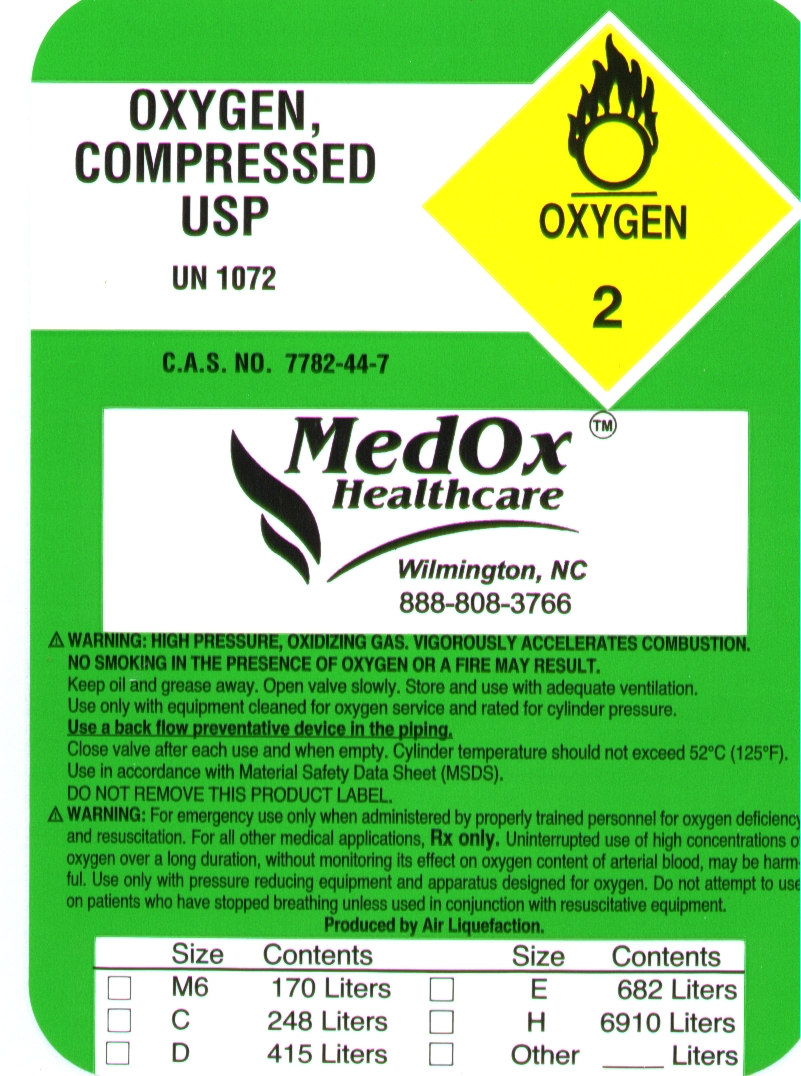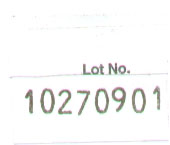 DRUG LABEL: OXYGEN
NDC: 65300-123 | Form: GAS
Manufacturer: Medox Healthcare
Category: prescription | Type: HUMAN PRESCRIPTION DRUG LABEL
Date: 20091028

ACTIVE INGREDIENTS: OXYGEN 210 mL/1 L

COMPRESSED OXYGEN LABEL AND LOT LABEL